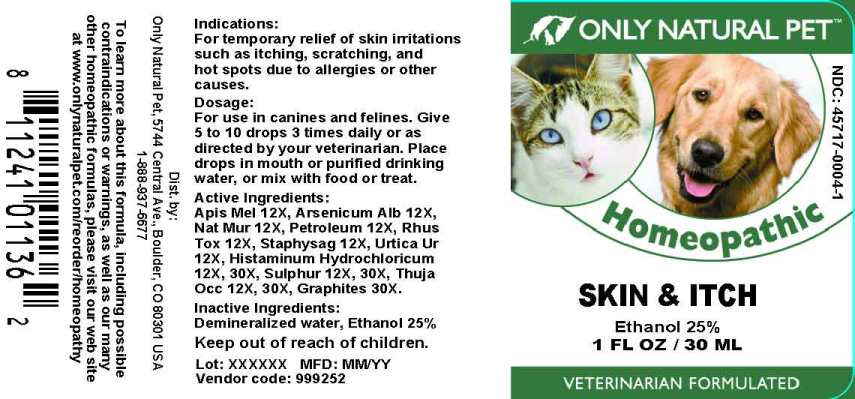 DRUG LABEL: Skin and Itch
NDC: 45717-0004 | Form: LIQUID
Manufacturer: Only Natural Pet Store
Category: homeopathic | Type: OTC ANIMAL DRUG LABEL
Date: 20241003

ACTIVE INGREDIENTS: APIS MELLIFERA 12 [hp_X]/1 mL; ARSENIC TRIIODIDE 12 [hp_X]/1 mL; SODIUM CHLORIDE 12 [hp_X]/1 mL; KEROSENE 12 [hp_X]/1 mL; TOXICODENDRON PUBESCENS LEAF 12 [hp_X]/1 mL; DELPHINIUM STAPHISAGRIA SEED 12 [hp_X]/1 mL; URTICA URENS WHOLE 12 [hp_X]/1 mL; HISTAMINE DIHYDROCHLORIDE 12 [hp_X]/1 mL; SULFUR 12 [hp_X]/1 mL; THUJA OCCIDENTALIS LEAF 12 [hp_X]/1 mL; GRAPHITE 30 [hp_X]/1 mL
INACTIVE INGREDIENTS: WATER; ALCOHOL

Drug Facts:

ACTIVE INGREDIENTS:

Apis Mellifica 12X, Arsenicum Album 12X, Natrum Muriaticum 12X, Petroleum 12X, Rhus Tox 12X, Staphysagria 12X, Urtica Urens 12X, Histaminum Hydrochloricum 12X, 30X, Sulphur 12X, 30X, Thuja Occidentalis 12X, 30X, Graphites 30X.

INDICATIONS:

For temporary relief of skin irritations such as itching, scratching, and hot spots due to allergies or other causes.

WARNINGS:

Keep out or reach of children.

KEEP OUT OF REACH OF CHILDREN:

DIRECTIONS:

For use in canines and felines. Give 5 to 10 drops 3 times daily or as directed by your veterinarian. Place drops in mouth or purified drinking water, or mix with food or treat.

INDICATIONS:

For temporary relief of skin irritations such as itching, scratching, and hot spots due to allergies or other causes.

INACTIVE INGREDIENTS:

Demineralized water, Ethanol 25%

QUESTIONS

Dist. by:

Only Natural Pet, 5744 Central Ave., Boulder, CO 80301 USA

1-888-937-6677

To learn more about this formula, including possible contraindications or warnings, as well as our many other homeopathic formulas, please visit our web site at www.only naturalpet.com/reorder/homeopathy

PACKAGE LABEL DISPLAY:

ONLY NATURAL PET
NDC: 45717-0004-1
Homeopathic
SKIN & ITCH
1 FL OZ / 30 ML